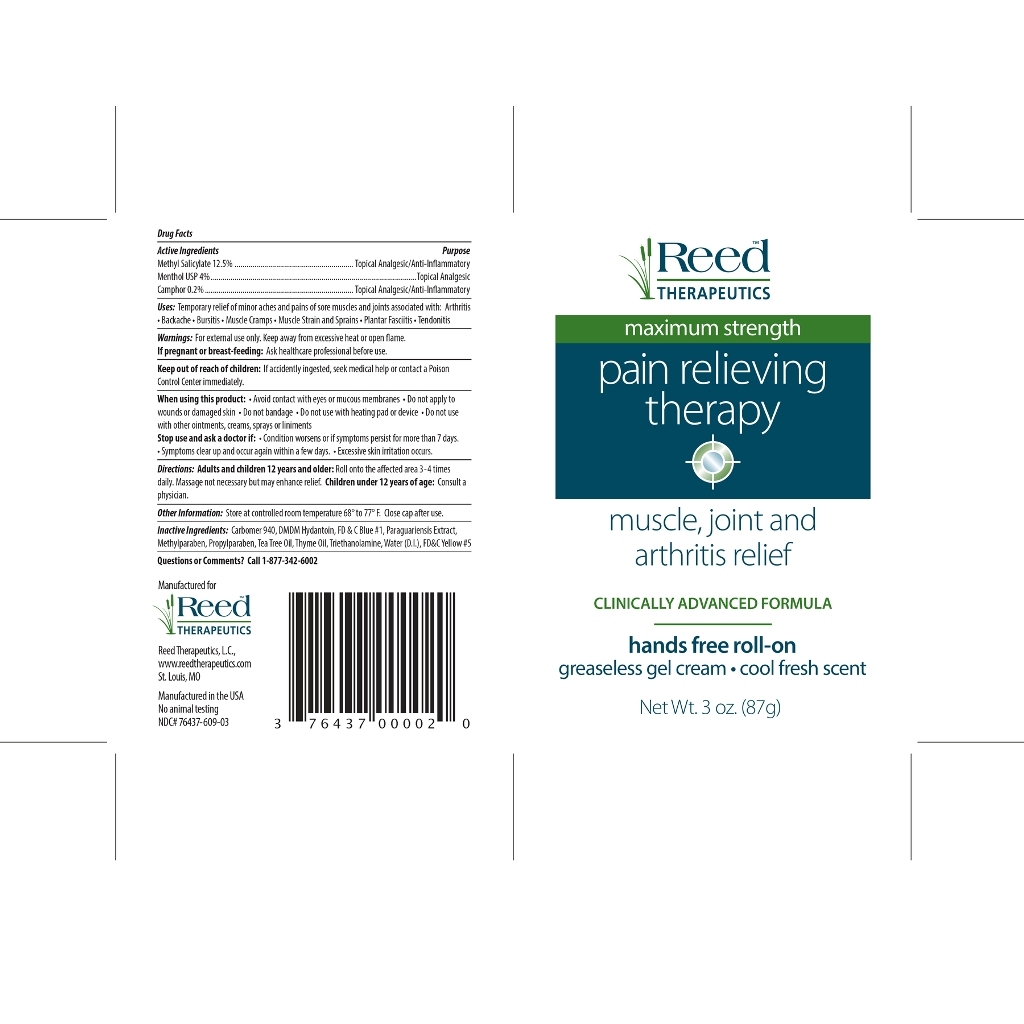 DRUG LABEL: Reed Therapeutics Pain Relieving Therapy
NDC: 76437-609 | Form: GEL
Manufacturer: Reed Therapeutics
Category: otc | Type: HUMAN OTC DRUG LABEL
Date: 20130329

ACTIVE INGREDIENTS: METHYL SALICYLATE 12.5 g/100 g; MENTHOL 4 g/100 g; CAMPHOR (SYNTHETIC) 0.2 g/100 g
INACTIVE INGREDIENTS: CARBOMER 940; DMDM HYDANTOIN; FD&C BLUE NO. 1; ILEX PARAGUARIENSIS WHOLE; METHYLPARABEN; PROPYLPARABEN; TEA TREE OIL; THYME OIL; TROLAMINE; WATER; FD&C YELLOW NO. 5

Reed Therapeutics Pain Relieving Therapy

Drug Facts

Active Ingredient, Purpose

Methyl Salicylate 12.5%, Topical Analgesic/Anti-Inflammatory

Menthol USP 4%, Topical Analgesic

Camphor 0.2%, Topical Analgesic, Anti-Inflammatory

Uses

Temporary relief of minor aches and pain of sore muscles and joints associated with: arthritis, backache, bursitis, muscle cramps, muscle strain and sprains, plantar fasciitis, tendonitis

Warnings

For external use only. Keep away from excessive heat or open flame.

If pregnant or breast-feeding: Ask healthcare professional before use.

Keep out of reach of children

If accidently ingested, seek medical help or contact Poison Control Center immediately.

When using this product

Avoid contact with eyes or mucous membranes

Do not apply to wounds or damaged skin

Do not bandage

Do not use with heating pad or device

Do not use with other ointments, cream, sprays, or liniments

Stop use and ask a doctor if

Condition worsens or if symptoms persist for more than 7 days

Symptoms clear up and occur again within a few days

Excessive skin irritation occurs

Directions

Adults and children 12 year and older: Gently massage and apply to affected area 3-4 times daily. Massage not necesssary but may enhance relief.

Children under 12 years of age: consult a physician.

Other Information

Store at controlled room temperture 68' to 77' F. Close cap after use.

Inactive Ingredients

Carbomer 940, DMDM Hydantoin, FD&C Blue #1, Paragurariensis Extract, Methylparaben, Propylparaben, Tea Tree oil, Thyme oil, Triethanolamine, Water(D.I), FD&C Yellow #5